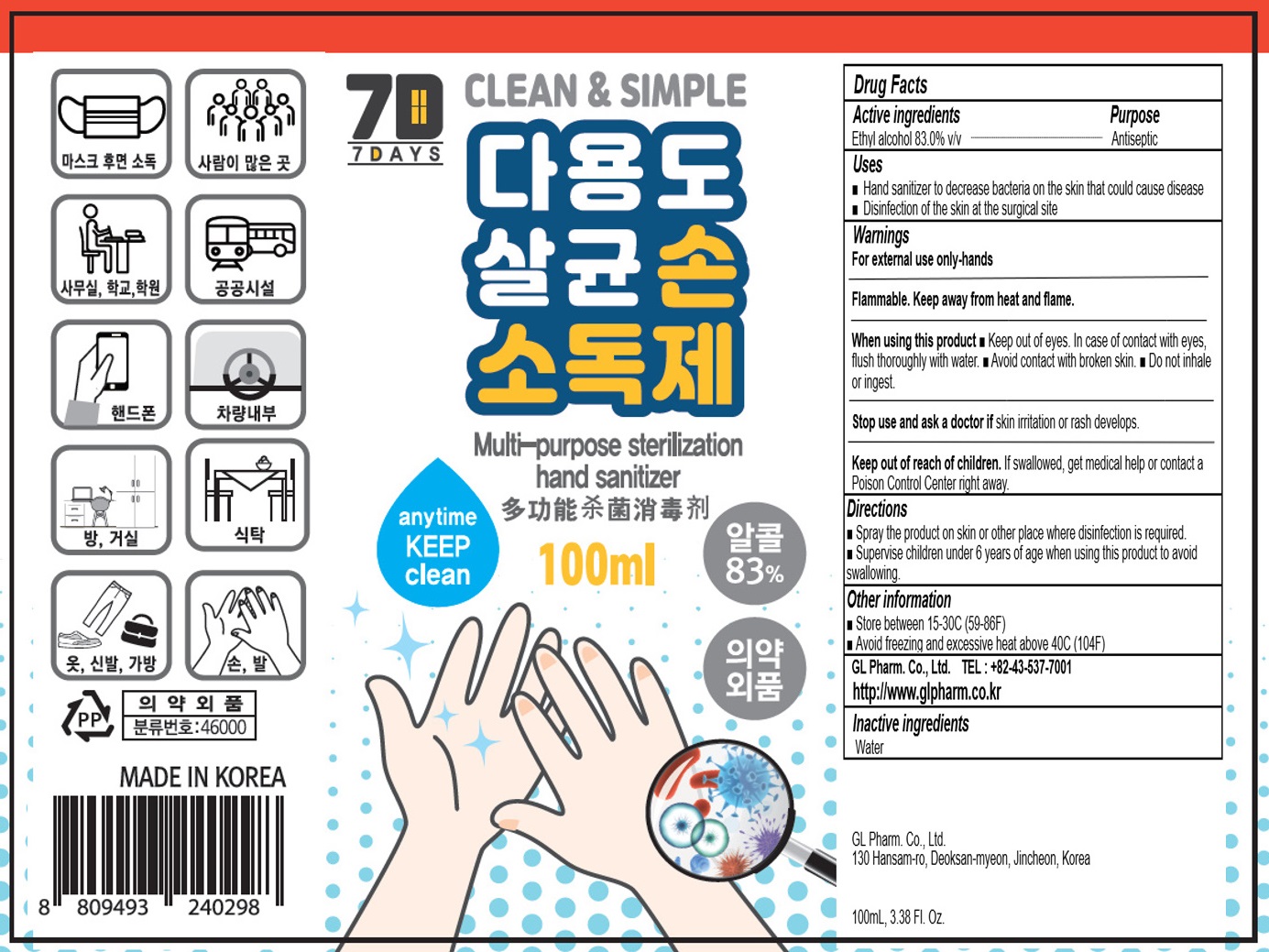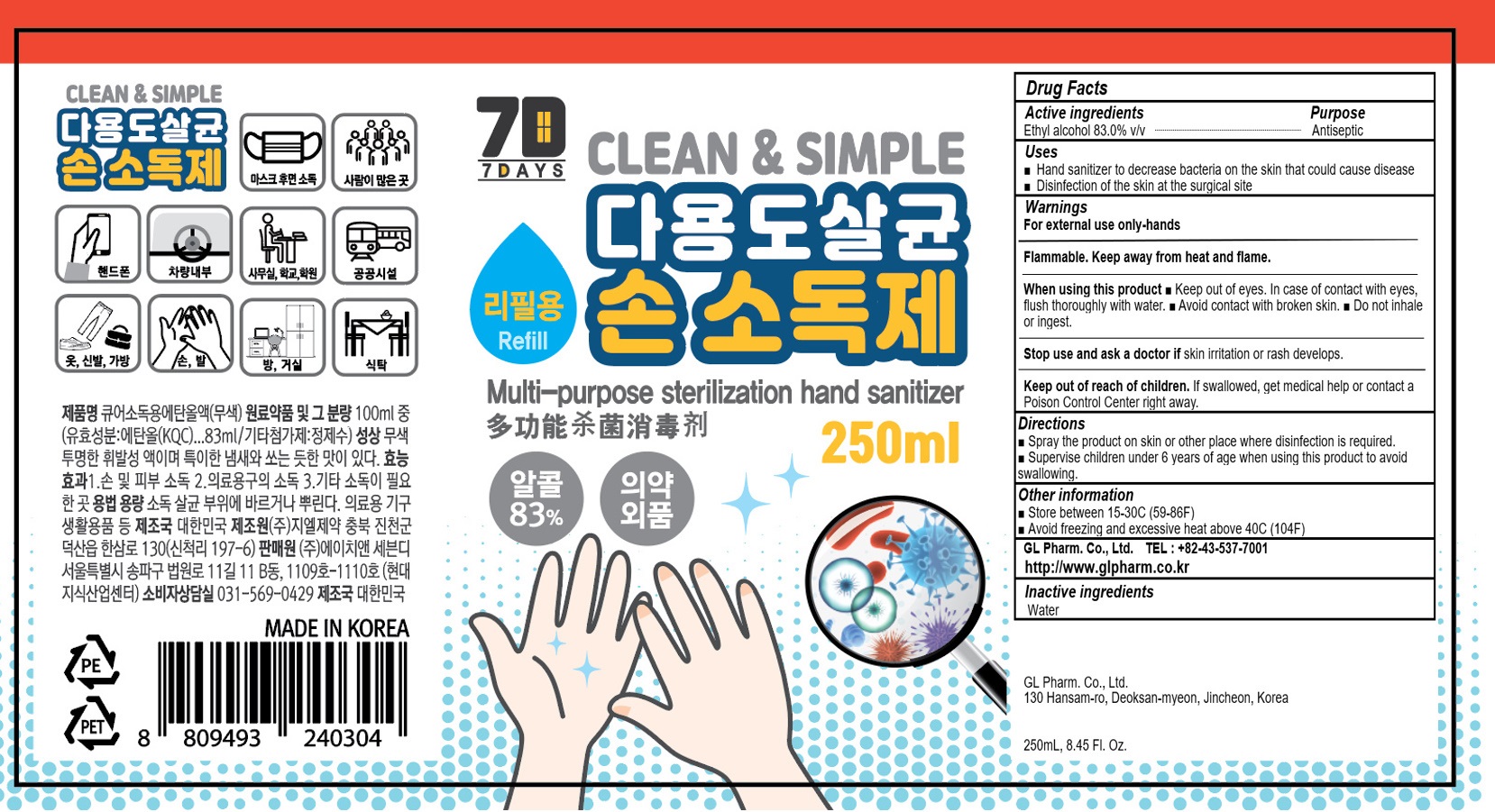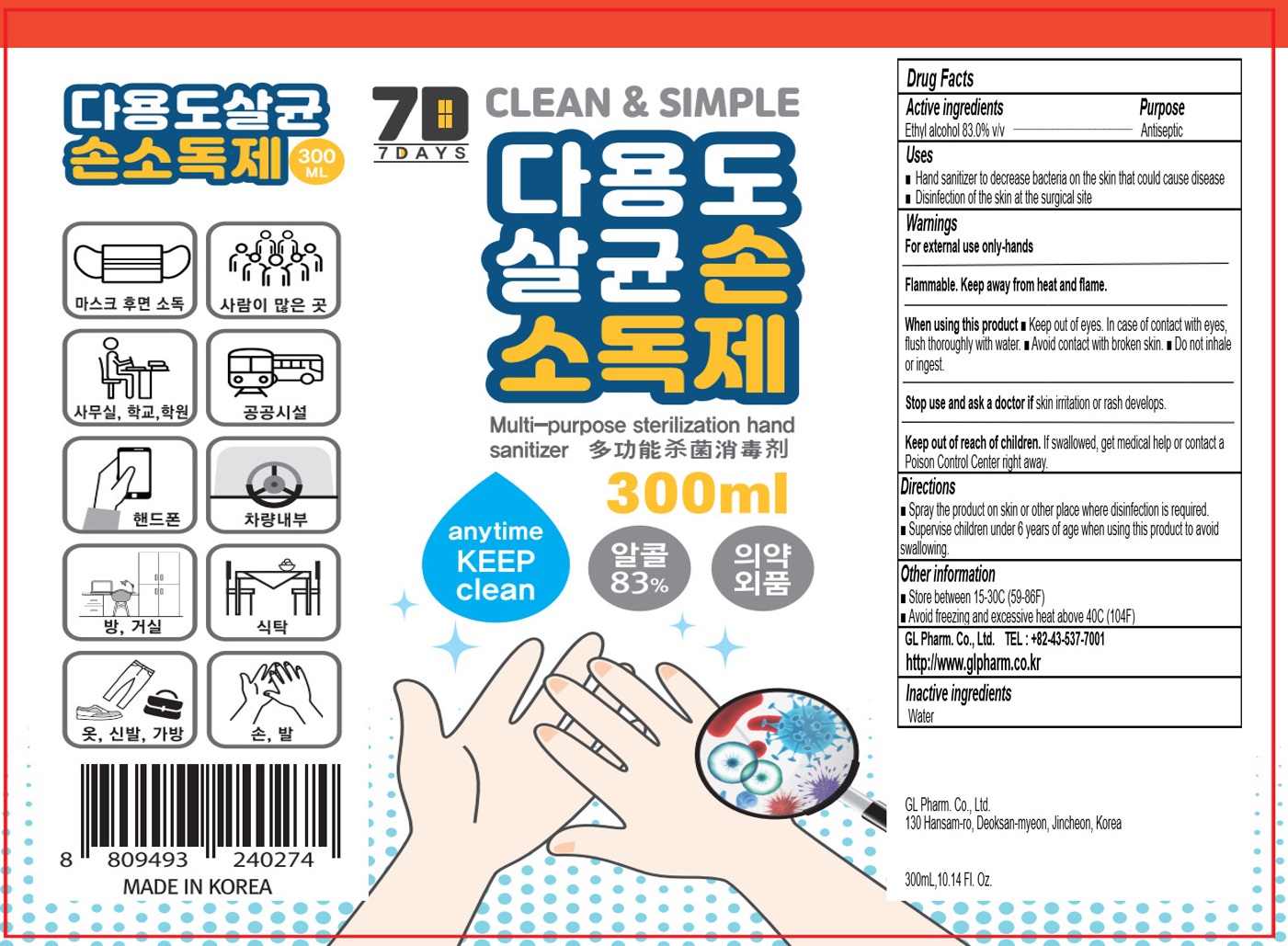 DRUG LABEL: Multi purpose sterilization hand sanitizer
NDC: 74713-0510 | Form: SPRAY
Manufacturer: GL Pharm. Co., Ltd.
Category: otc | Type: HUMAN OTC DRUG LABEL
Date: 20200504

ACTIVE INGREDIENTS: ALCOHOL 83 mL/100 mL
INACTIVE INGREDIENTS: Water

ACTIVE INGREDIENT

Active ingredients: Ethyl alcohol 83.0% v/v

INACTIVE INGREDIENT

Inactive ingredients:

Water

PURPOSE

Purpose: ANTISEPTIC

WARNINGS

For external use only-hands

Flammable. Keep away from heat and flame.

When using this product ■ Keep out of eyes. In case of contact with eyes,
flush thoroughly with water. ■ Avoid contact with broken skin. ■ Do not inhale
or ingest.

Stop use and ask a doctor if skin irritation or rash develops.

Keep out of reach of children. If swallowed, get medical help or contact a Poison Control Center right away.

Uses

■ Hand sanitizer to decrease bacteria on the skin that could cause disease
■ Disinfection of the skin at the surgical site

Directions

■ Spray the product on skin or other place where disinfection is required.
■ Supervise children under 6 years of age when using this product to avoid swallowing.

Other information

• Store between 15-30C (59-86F)
• Avoid freezing and excessive heat above 40C (104F)

Questions

http://www.glpharm.co.kr or TEL : +82-43-537-7001